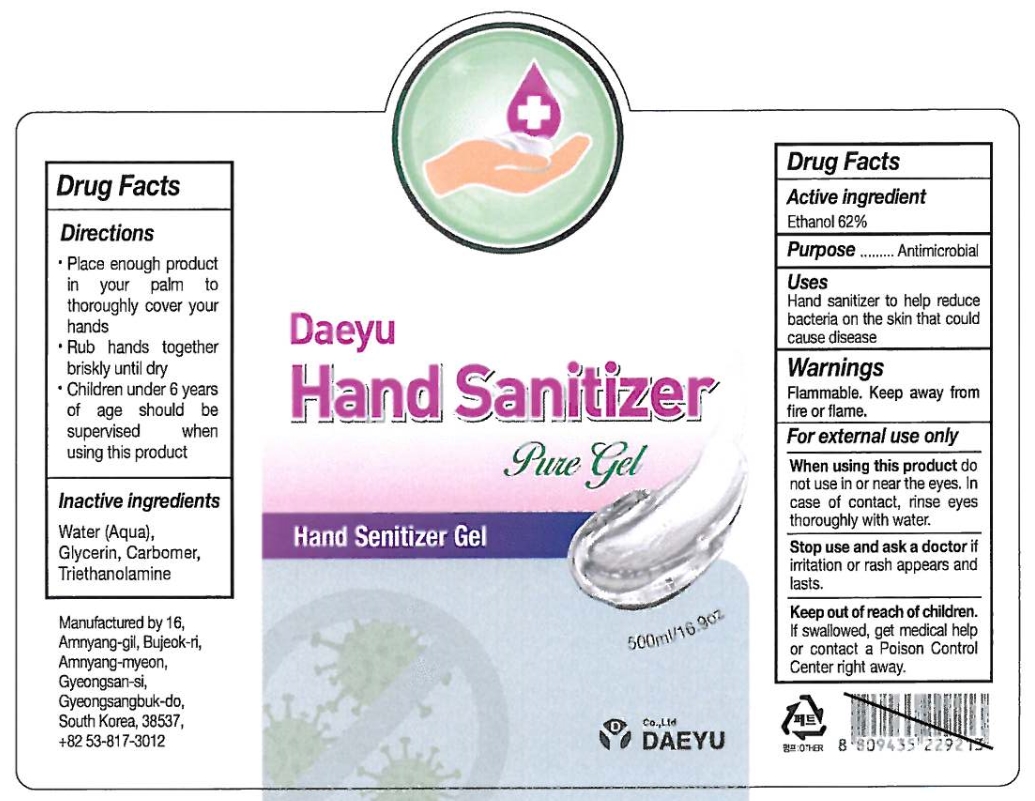 DRUG LABEL: Daeyu Hand Sanitizer Pure Gel
NDC: 79548-201 | Form: GEL
Manufacturer: Dae Yu Co., Ltd
Category: otc | Type: HUMAN OTC DRUG LABEL
Date: 20200714

ACTIVE INGREDIENTS: ALCOHOL 62 mL/100 mL
INACTIVE INGREDIENTS: GLYCERIN; CARBOMER HOMOPOLYMER, UNSPECIFIED TYPE; WATER; TROLAMINE

79548-201

Active Ingredient

Ethanol 62%

Purpose

Antimicrobial

Uses

Hand sanitizer to help reduce bacteria on the skin that could cause disease.

Warnings

Flammable. Keep away from fire or flame.

For external use only.

When using this product

do not use in or near the eyes. In case of contact, rinse eyes thoroughly with water.

Stop use and ask a doctor

if irritation or rash appears and lasts.

Keep out of reach of children.

If swallowed, get medical help or contact a Poison Control Center right away.

Directions

- Place enough product in your palm to thoroughly cover your hands
- Rub hands together briskly until dry
- Children under 6 years of age should be supervised when using this product

Inactive ingredients

Water, Glycerin, Carbomer, Triethanolamine